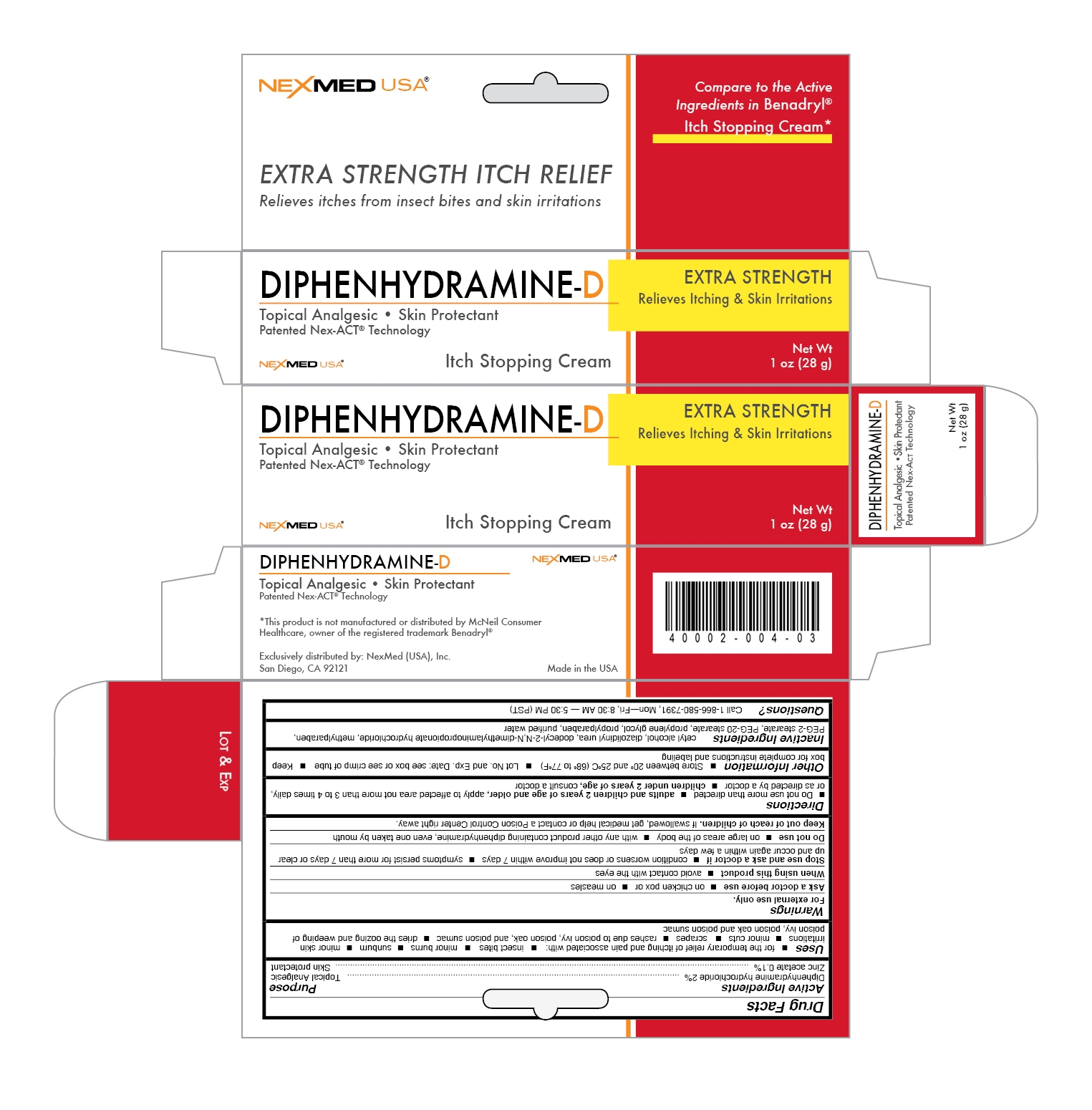 DRUG LABEL: Diphenhydramine 
NDC: 40002-004 | Form: CREAM
Manufacturer: NexMed (USA), Inc.
Category: otc | Type: HUMAN OTC DRUG LABEL
Date: 20110829

ACTIVE INGREDIENTS: DIPHENHYDRAMINE HYDROCHLORIDE     2 g/100 g; ZINC ACETATE     .1 g/100 g
INACTIVE INGREDIENTS: CETYL ALCOHOL    ; DIAZOLIDINYL UREA; Dodecyl-2-N,N-Dimethylaminopropionate Hydrochloride  ; METHYLPARABEN; PEG-2 STEARATE; PEG-20 STEARATE    ; PROPYLENE GLYCOL    ; PROPYLPARABEN; WATER

Drug Facts

Active Ingredients

Diphenhydramine hydrochloride 2%

Zinc acetate 0.1%

Purpose

Topical Analgesic

Skin protectant

Uses

- For the temporary relief of itching and pain associated with:
- insect bites
- minor burns
- sunburn
- minor skin irritations
- minor cuts
- scrapes
- rashes due to poison ivy, poison oak, and poison sumac
- dries the oozing and weeping of poison ivy, poison oak, and poison sumac

Warnings

For external use only.

Ask a doctor before use

- on chicken pox
- on measles

When using this product

- avoid contact with the eyes

Stop use and ask a doctor if

condition worsens or does not improve within 7 days, or symptoms persist for more than 7 days or clear up and occur again within a few days.

Do not use

- on large areas of the body
- with any other product containing diphenhydramine, even one taken by mouth

Keep out of reach of children.

If swallowed, get medical help or contact a Poison Control Center right away.

Directions

- do not use more than directed
- adults and children 2 years of age and older, apply to affected area not more than 3 to 4 times daily, or as directed by a doctor
- children under 2 years of age, consult a doctor

Other information

- Store between 20o and 25oC (68o to 77oF)
- Lot no. and Exp. Date: see box or see crimp of tube
- Keep box for complete instructions and labeling

Inactive Ingredients

cetyl alcohol, diazolidinyl urea, dodecyl-2-N,N-dimethylaminopropionate hydrochloride, methylparaben, PEG-2 stearate, PEG-20 stearate, propylene glycol, propylparaben, purified water

QUESTIONS

Call 1-866-580-7391, Mon - Fri, 8:30 AM - 5:30 PM (PST)